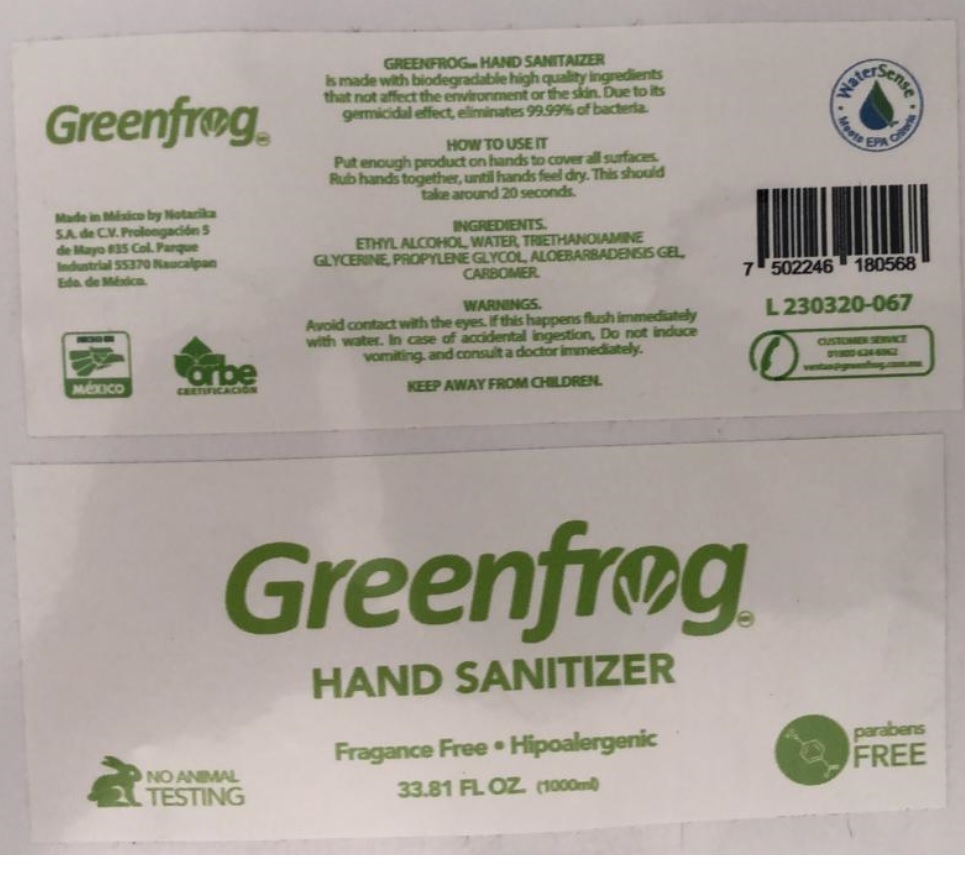 DRUG LABEL: Greenfrog HAND SANITIZER
NDC: 77031-454 | Form: LIQUID
Manufacturer: Frozen Wheels, Llc
Category: otc | Type: HUMAN OTC DRUG LABEL
Date: 20200508

ACTIVE INGREDIENTS: ALCOHOL 0.75 L/1 L
INACTIVE INGREDIENTS: WATER; TROLAMINE; GLYCERIN; PROPYLENE GLYCOL; ALOE VERA LEAF; CARBOMER HOMOPOLYMER, UNSPECIFIED TYPE

Greenfrog HAND SANITIZER

PURPOSE

Antiseptic

INDICATIONS AND USAGE

Hand Sanitizer

HOW TO USE IT

Put enough product on hands to cover all surfaces. Rub hands together, until hands feel dry. This should take around 20 seconds

INGREDIENTS.

ETHYL ALCOHOL

INACTIVE INGREDIENT

WATER, TRIETHANOIMINE, GLYCERINE, PROPYLENE GLYCOL, ALOE BARBADENSIS GEL, CARBOMER

WARNINGS.

Avoid contact with the eyes. If this happens flush immediately with water. In case of accidental ingestion, Do not induce vomiting. and consult a doctor immediately.

Fragance Free • Hipoalergenic

NO ANIMAL TESTING

parabens FREE

Made in México by Notarika

S.A. de. CV Prolongación 5

de Mayo 35 Col. Parque

Industrial 55370 Naucalpan

Exo de Mexico.

orbe CERTIFICATION

GREENFROG HAND SANITIZER

is made with biodegradable high quality ingredients that not affect the environment or the skin. Due to its germicidal effect, eliminates 99.99% of bacteria.

WaterSense • Meets EPA Criteria